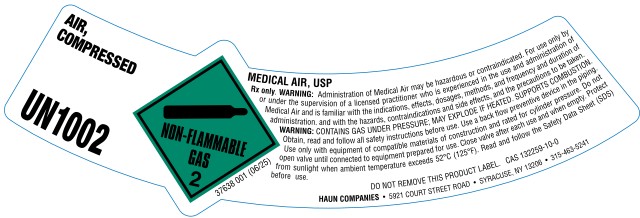 DRUG LABEL: Air
NDC: 14961-004 | Form: GAS
Manufacturer: Haun Specialty Gases, Inc.
Category: prescription | Type: HUMAN PRESCRIPTION DRUG LABEL
Date: 20251229

ACTIVE INGREDIENTS: OXYGEN 210 mL/1 L
INACTIVE INGREDIENTS: NITROGEN 790 mL/1 L

Air

PACKAGE LABEL

AIR, COMPRESSED UN1002 NON-FLAMMABLE GAS 2 MEDICAL AIR, USP
RX only. WARNING: Administration of Medical Air may be hazardous or contraindicated. For use only by or under the supervision of licensed practitioner who is experienced in the use and administration of Medical Air and is familiar with the indications, effects, dosages, methods, and frequency and duration of administration, and with the hazards, contraindications and side effects, and the precautions to be taken.
WARNING: CONTAINS GAS UNDER PRESSURE; MAY EXPLODE IF HEATED. SUPPORTS COMBUSTION. Do not handle until all safety precautions have been read and understood. Use a back flow preventive device in the piping. Use only with equipment of compatible materials of construction and rated for cylinder pressure. Close valve ager each use and when empty. Protect from sunlight when ambient temperature exceeds 52 degrees C (125 degrees F). Read and follow the Safety Data Sheet (SDS) before use.
CAS 132259-10-0 DO NOT REMOVE THIS PRODUCT LABEL
HAUN COMPANIES 5921 COURT STREET ROAD . SYRACUSE, NY 13206 315-463-5241